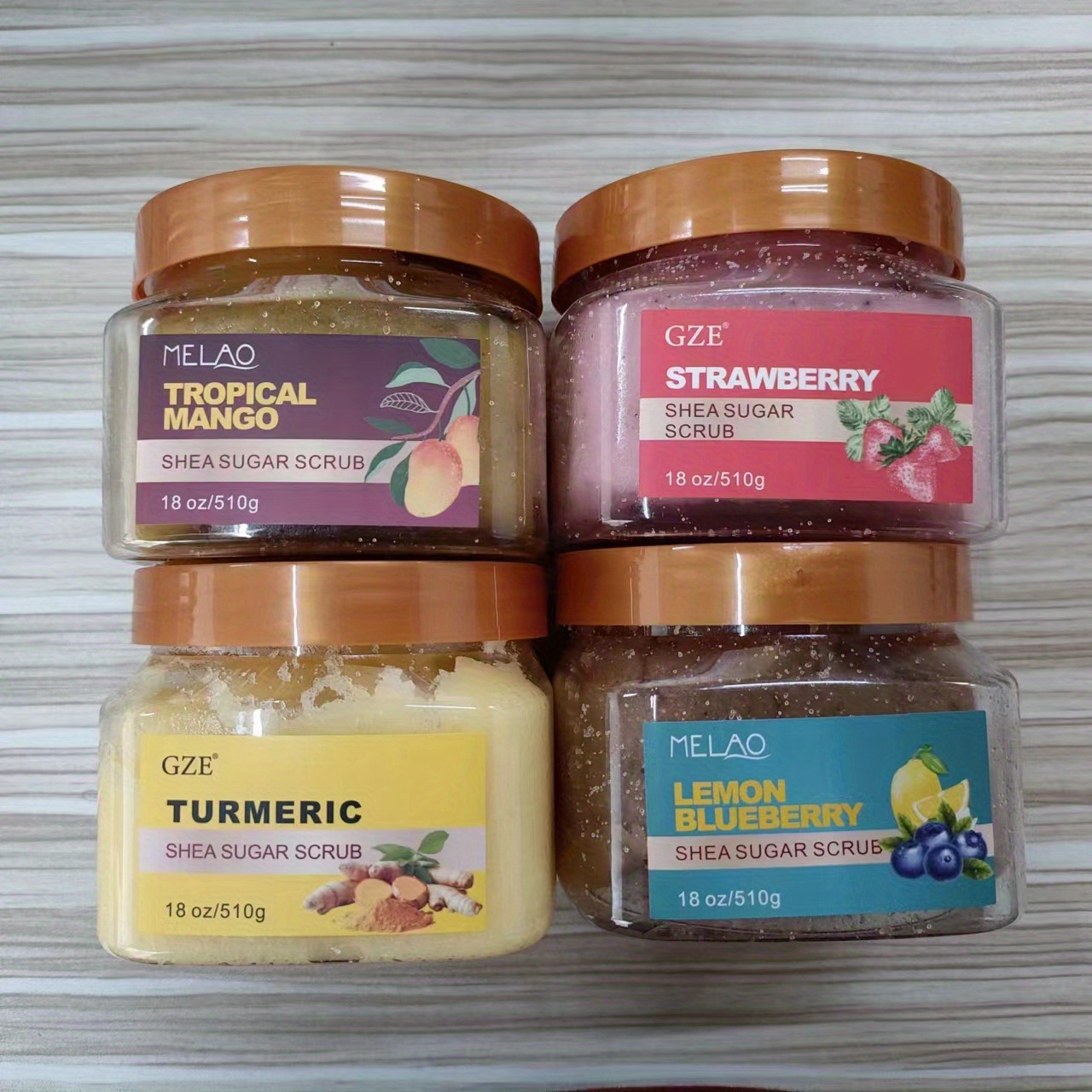 DRUG LABEL: MELAO SHEA SUGAR SCRUB
NDC: 74458-333 | Form: GRANULE
Manufacturer: Guangzhou Yilong Cosmetics Co., Ltd
Category: otc | Type: HUMAN OTC DRUG LABEL
Date: 20241109

ACTIVE INGREDIENTS: ASCORBIC ACID 2 g/100 g; COCONUT SHELL 2 g/100 g
INACTIVE INGREDIENTS: GLYCERIN; SUCROSE; BUTYROSPERMUM PARKII (SHEA) BUTTER; FRAGRANCE 13576

ACTIVE INGREDIENT

Ascorbic Acid

Coconut Shell

INACTIVE INGREDIENT

Sucrose

Glycerin

Butyrospermum Parkii (Shea) Butter

Fragrance

PURPOSE

Exfoliating.

WARNINGS

For external use only.

Stop use and ask a doctor if rash occurs.

INDICATIONS AND USAGE

After washing your body, take an appropriate amount of scrub and apply it to the hand joints, knee joints, ankle joints and other parts of the body with a lot of keratin, rub in a circular motion for 2-3 minutes, and finally rinse off with water.

When using this product keep out of eyes. Rinse with water to remove.

Do not use on damaged or broken skin

Keep out of reach of children. If swallowed, get medical help or contact a Poison Control Center right away.

DOSAGE AND ADMINISTRATION

After washing your body, take an appropriate amount of scrub and apply it to the hand joints, knee joints, ankle joints and other parts of the body with a lot of keratin, rub in a circular motion for 2-3 minutes, and finally rinse off with water. Twice a week.